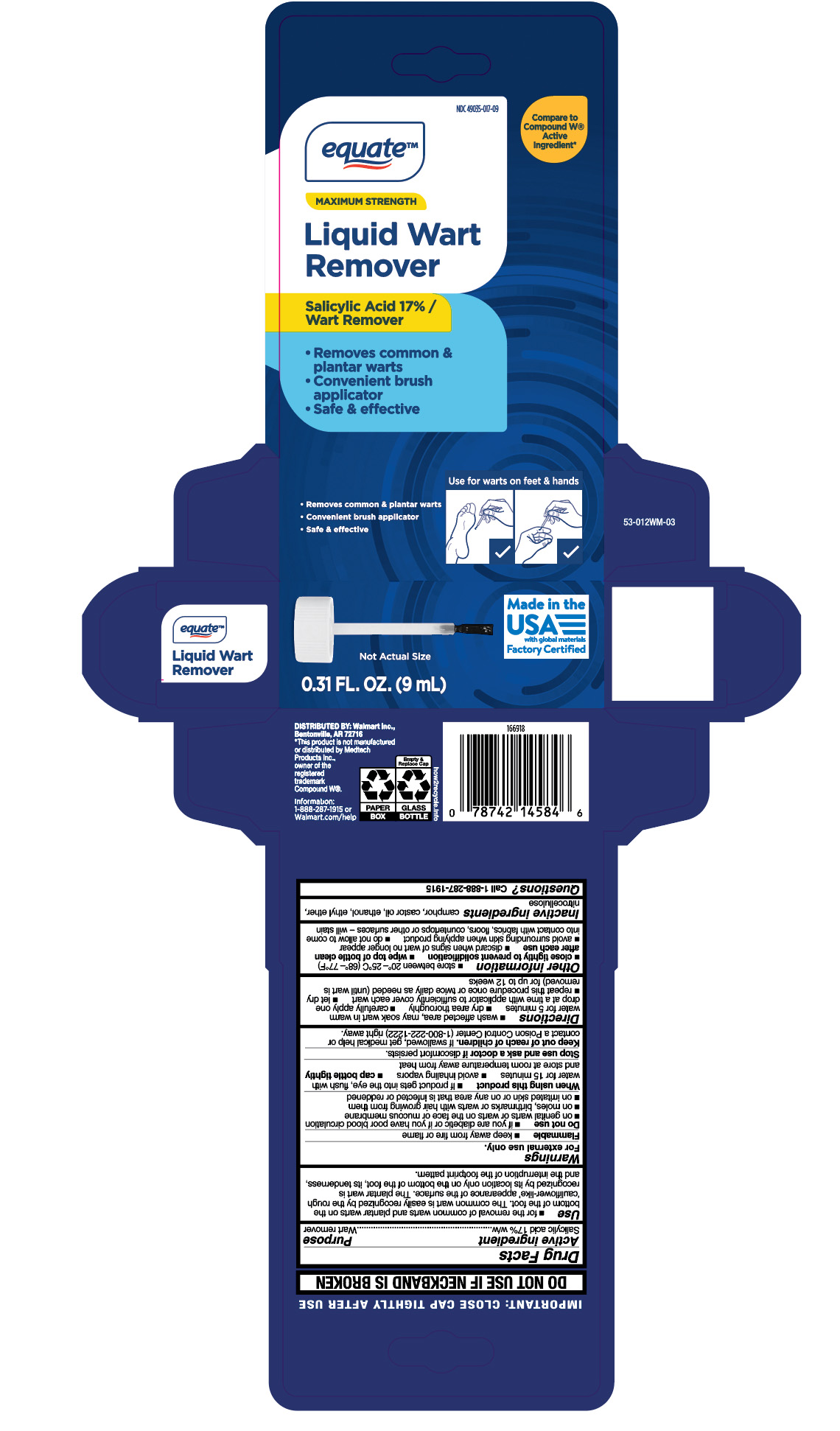 DRUG LABEL: Maximum Strength Wart Remover with Salicylic Acid
NDC: 49035-017 | Form: LIQUID
Manufacturer: Wal-Mart Stores, Inc.
Category: otc | Type: HUMAN OTC DRUG LABEL
Date: 20260202

ACTIVE INGREDIENTS: SALICYLIC ACID 17 mg/100 mg
INACTIVE INGREDIENTS: ALCOHOL; ETHYL ETHER; PYROXYLIN; CAMPHOR (NATURAL); CASTOR OIL

Equate Maximum Strength Liquid Wart Remover

Active ingredient

Salicylic acid 17%w/w

Purpose

Wart remover

Uses

- for the removal of common warts and plantar warts on the bottom of the foot. The common wart is easily recognized by the rough 'cauliflower-like' appearance of the surface. The plantar wart is recognized by its location only on the bottom of the foot, its tenderness, and the interruption of the footprint pattern.

Warnings

For external use only.

Flammable

- keep away from fire or flame

Do not use

- if you are diabetic or if you have poor blood circulation
- on genital warts or warts on the face or mucous membrane
- on moles, birthmarks or warts with hair growing from them
- on imitated skin or on any area that is infected or reddened

When using this product

- If product gets into the eye, flush with water for 15 minutes
- avoid inhaling vapors
- cap bottle tightly
- and store at room temperature away from heat

Stop use and ask doctor if

discomfort persists.

Keep out of reach of children.

If swallowed, get medical help or contact a Poison Control Center (1-800-222-1222) right away.

Directions

- wash affected area, may soak wart in warm water for 5 minutes
- dry area thoroughly
- carefully apply one drop at a time with applicator to sufficiently cover each wart
- let dry
- repeat this procedure once or twice daily as needed (until wart is removed) for up to 12 weeks

Other information

- store between 20°-25°C (68°-77°F)
- close tightly to prevent solidification
- wipe top of bottle clean after each use
- discard when signs of wart no longer appear
- avoid surrounding skin when applying product
- do not allow to come into contact with fabrics, floors, countertops or other surfaces - will stain

Inactive ingredients

camphor, castor oil, ethanol, ethyl ether, nitrocellulose

Questions?

1-888-287-1915

RECENT MAJOR CHANGES

.

Principal Display Panel

equate

MAXIMUM STRENGTH

Liquid Wart

Remover

Salicylic Acid 17% /

Wart Remover

- Removes common &

plantar warts

- Convenient brush

applicator

- Safe & effective

0.31 FL. OZ. (9 mL)